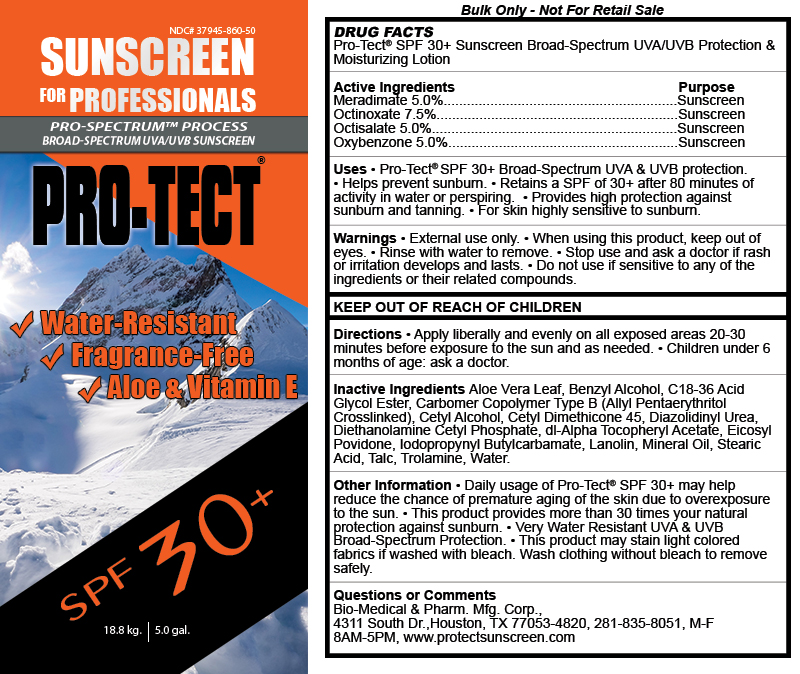 DRUG LABEL: Pro-Tect Sunscreen for Professionals
NDC: 37945-860 | Form: LOTION
Manufacturer: Bio-Medical & Pharmaceutical Manufacturing Corporation
Category: otc | Type: HUMAN OTC DRUG LABEL
Date: 20200205

ACTIVE INGREDIENTS: OCTINOXATE 75 mg/1 g; MERADIMATE 50 mg/1 g; OXYBENZONE 50 mg/1 g; OCTISALATE 50 mg/1 g
INACTIVE INGREDIENTS: WATER; ALOE VERA LEAF; LANOLIN; IODOPROPYNYL BUTYLCARBAMATE; STEARIC ACID; MINERAL OIL; TALC; TROLAMINE; BENZYL ALCOHOL; CARBOMER COPOLYMER TYPE B (ALLYL PENTAERYTHRITOL CROSSLINKED); CETYL ALCOHOL; CETYL DIMETHICONE 45; DIAZOLIDINYL UREA; DIETHANOLAMINE CETYL PHOSPHATE; .ALPHA.-TOCOPHEROL ACETATE, DL-; EICOSYL POVIDONE

Active ingredients

Meradimate 5.0%

Octinoxate 7.5%

Octisalate 5.0%

Oxybenzone 5.0%

Purpose

Sunscreen

Uses

• Pro-Tect® SPF 30+ Broad-Spectrum UVA & UVB protection. • Helps prevent sunburn. • Retains a SPF of 30+ after 80 minutes of activity in water or perspiring. • Provides high protection against sunburn and tanning. • For skin highly sensitive to sunburn.

Warnings

• External use only. • When using this product, keep out of eyes. • Rinse with water to remove. • Stop use and ask a doctor if rash or irritation develops and lasts. • Do not use if sensitive to any of the ingredients or their related compounds.

KEEP OUT OF REACH OF CHILDREN

Directions

•Apply this product topically to affected areas and allow to dry without rubbing. •Use up to 3 times daily. •Use only as directed.

Inactive Ingredients

Aloe Vera Leaf, Benzyl Alcohol, C18-36 Acid Glycol Ester, Carbomer Copolymer Type B (Allyl Pentaerythritol Crosslinked), Cetyl Alcohol, Cetyl Dimethicone 45, Diazolidinyl Urea, Diethanolamine Cetyl Phosphate, dl-Alpha Tocopheryl Acetate, Eicosyl Povidone, Iodopropynyl Butylcarbamate, Lanolin, Mineral Oil, Stearic Acid, Talc, Trolamine, Water.

Other Information

• Daily usage of Pro-Tect® SPF 30+ may help reduce the chance of premature aging of the skin due to overexposure to the sun. • This product provides more than 30 times your natural protection against sunburn. • Very Water Resistant UVA & UVB Broad-Spectrum Protection. • This product may stain light colored fabrics if washed with bleach. Wash clothing without bleach to remove safely.

Questions or Comments

Bio-Medical & Pharm. Mfg. Corp., 4311 South Dr.,Houston, TX 77053-4820, 281-835-8051, M-F 8AM-5PM, www.protectsunscreen.com

Package label

SUNSCREEN FOR PROFESSIONALS

PRO-SPECTRUM PROCESS BROAD-SPECTRUM UVA/UVB SUNSCREEN

PRO-TECT

Water-Resistant

Fragrance-Free

Aloe & vitamin E

SPF 30+

18.8 kg /5 gal.